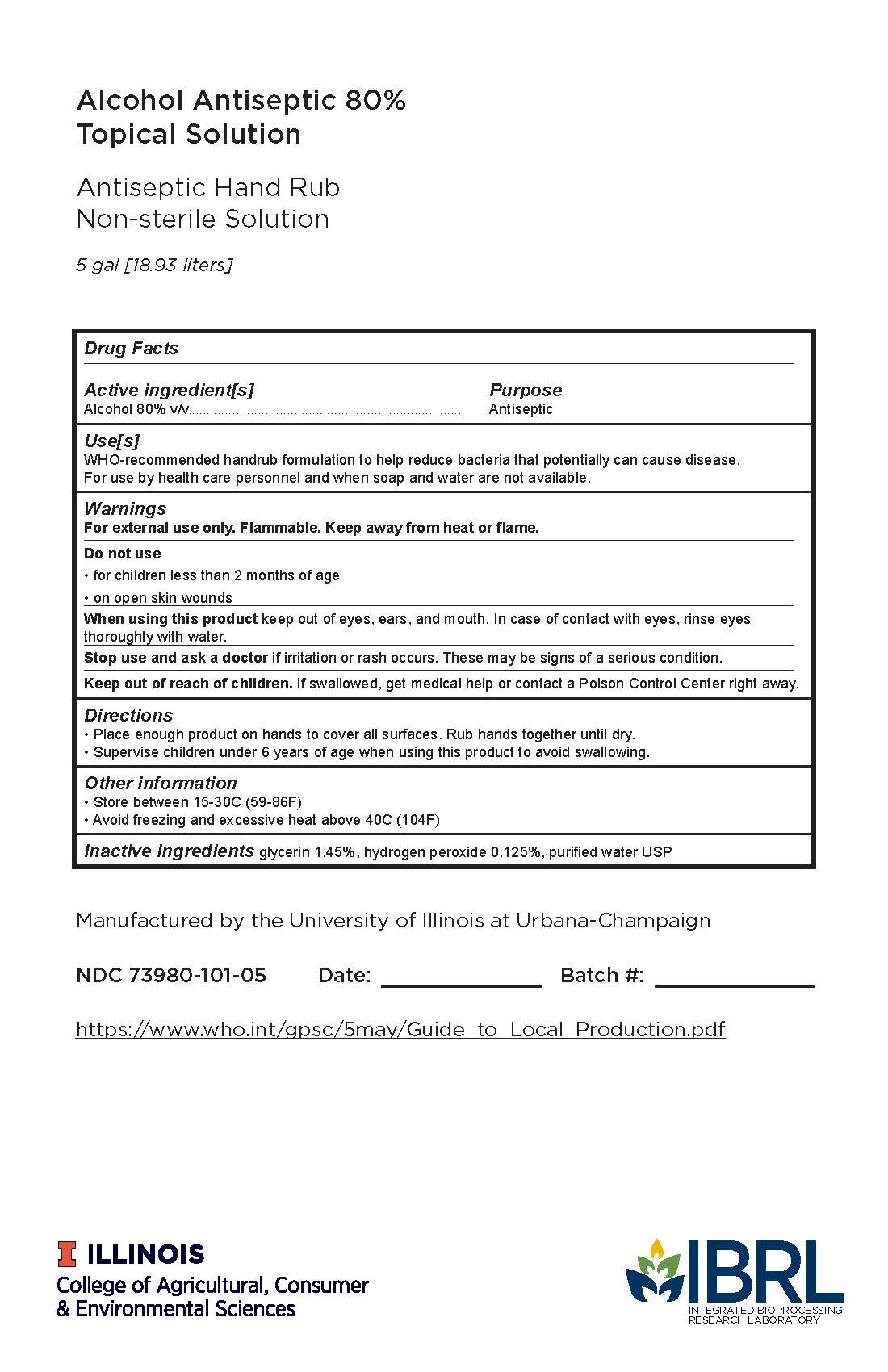 DRUG LABEL: Hand Sanitizer
NDC: 73980-101 | Form: GEL
Manufacturer: University Of Illinois
Category: otc | Type: HUMAN OTC DRUG LABEL
Date: 20201215

ACTIVE INGREDIENTS: ALCOHOL 0.8 mL/1 mL
INACTIVE INGREDIENTS: GLYCERIN 0.0145 mL/1 mL; HYDROGEN PEROXIDE 0.00125 mL/1 mL; WATER 0.18425 mL/1 mL

Alcohol Antiseptic 80% Topical Solution